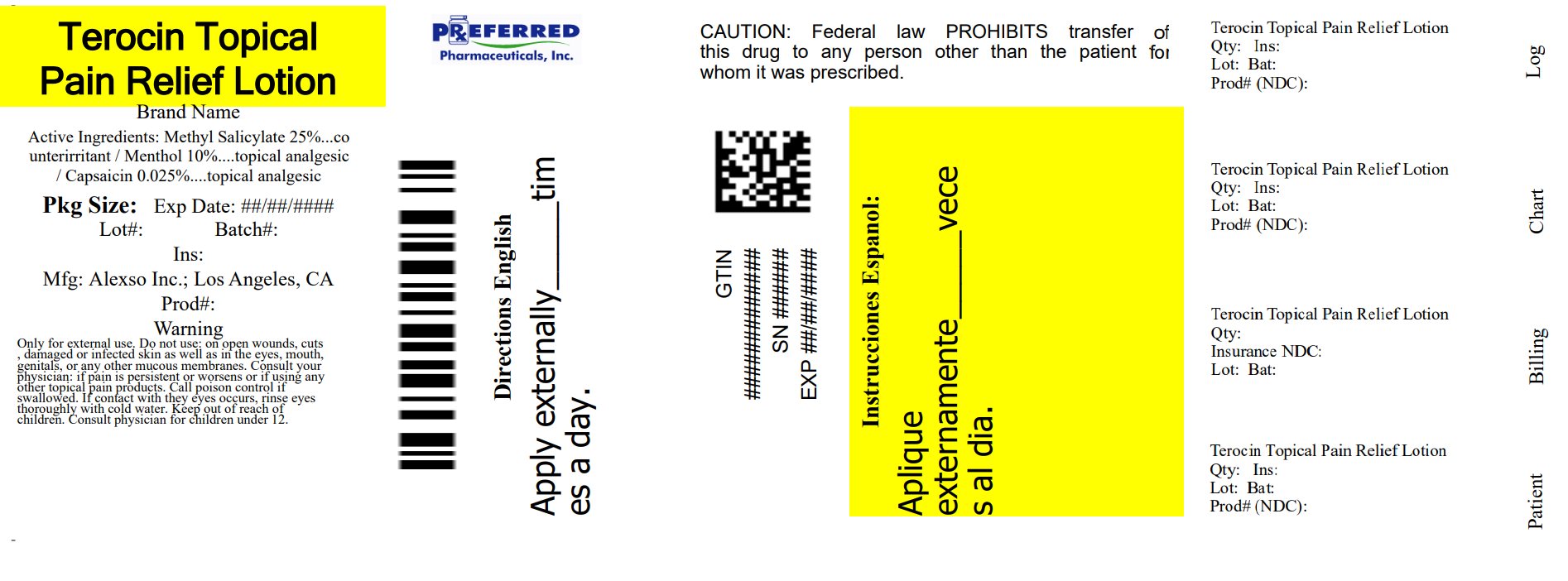 DRUG LABEL: New Terocin
NDC: 68788-7821 | Form: LOTION
Manufacturer: Preferred Pharmaceuticals Inc.
Category: otc | Type: HUMAN OTC DRUG LABEL
Date: 20250930

ACTIVE INGREDIENTS: METHYL SALICYLATE 25 g/100 mL; CAPSAICIN 0.025 g/100 mL; MENTHOL, UNSPECIFIED FORM 10 g/100 mL
INACTIVE INGREDIENTS: WATER; PROPYLENE GLYCOL; CETYL ALCOHOL; STEARIC ACID; GLYCERYL MONOSTEARATE; PEG-100 MONOSTEARATE; DIMETHYL SULFONE; LIDOCAINE; LAVENDER OIL; ALOE VERA LEAF; BORAGE SEED OIL; INDIAN FRANKINCENSE; XANTHAN GUM; TROLAMINE; METHYLPARABEN; PROPYLPARABEN; DMDM HYDANTOIN; IODOPROPYNYL BUTYLCARBAMATE

New Terocin Topical Pain Relief Lotion

Active ingredients:

Methyl Salicylate 25%
Capsaicin 0.025%
Menthol 10%

Purpose

Topical Analgesic

Uses:

Temporarily relieves mild aches and pains of muscles or joints.

Warnings

Only for external use.

Do Not Use:

on open wounds, cuts, damaged or infected skin as well as in the eyes, mouth, genitals, or any other mucous membranes.

Consult your physician:

if pain is persistent or worsens or if using any other topical pain products.

Keep out of reach of children.

Consult physician for children under 12.

Directions:

Wash and dry affected area. Shake bottle well before each use and gently rub over area of pain. Use is not recommended more than four times a day. Wash hands immediately afterwards to avoid contact with eyes.

Inactive Ingredients:

Aloe Barbadensis Leaf (Aloe Vera Gel) Juice, Aqua (Deionized Water), Borago Officinalis (Borage) Seed Oil, Boswellia Serrata Extract, C12-15 Alkyl Benzoate, Cetearyl Alcohol, Cetyl Alcohol, Diazolidinyl Urea, Dimethyl Sulfone (DMSO), DMDM Hydantoin, Glyceryl Stearate, Lavandula Angustifolia (Lavender) Oil, Methyl Paraben, PEG-100 Stearate, Polysorbate-20, Polysorbate-60, Propyl Paraben, Propylene Glycol, Stearic Acid, Stearyl Alcohol, Triethanolamine, Xanthan Gum.

Package/Label Principal Display Panel

NDC 68788-7821-1

New Terocin

Topical Pain
Relief Lotion

Long Lasting
Soothing Effect

120 ml (4 fl oz.)

Manufactured for: Alexso Inc.
Los Angeles, CA 90064

Store in a dry, cool place

Made in U.S.A.
Patent Pending

For Comments or Questions,
call 888-495-6075

Relabeled By: Preferred Pharmaceuticals Inc.

Label